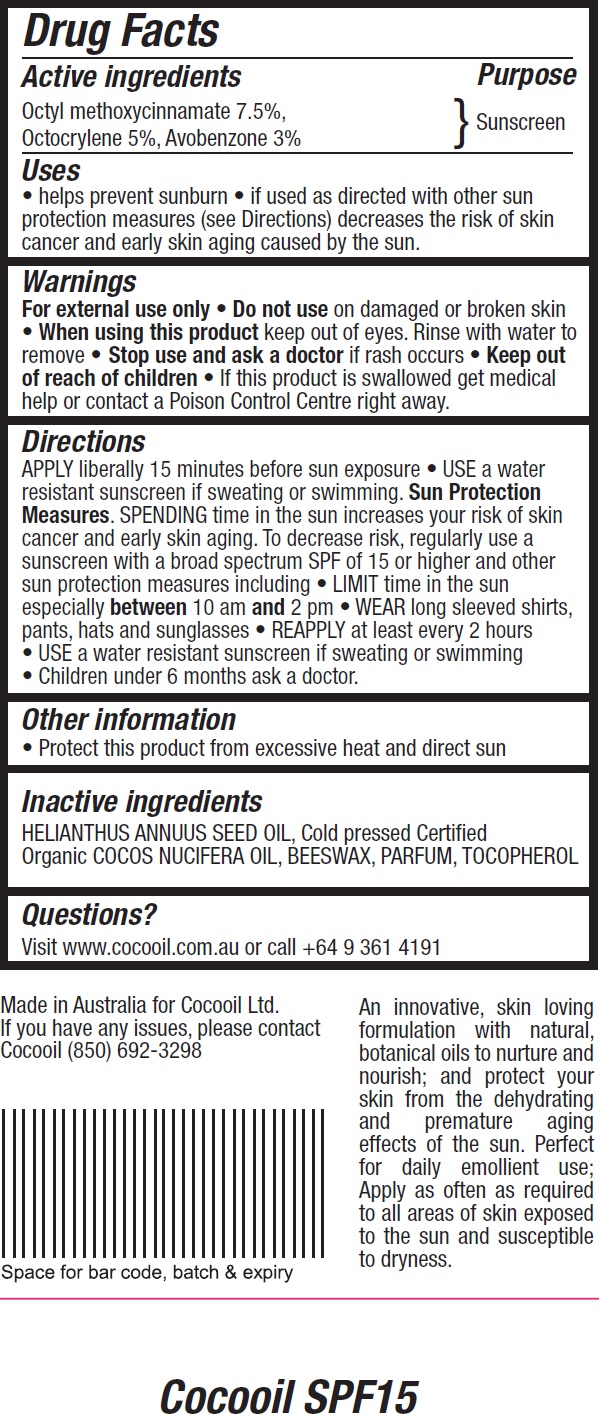 DRUG LABEL: COCOOIL SPF 15
NDC: 72645-015 | Form: LOTION
Manufacturer: Cocooil Limited
Category: otc | Type: HUMAN OTC DRUG LABEL
Date: 20181031

ACTIVE INGREDIENTS: OCTINOXATE 75 mg/1 mL; OCTOCRYLENE 50 mg/1 mL; AVOBENZONE 30 mg/1 mL
INACTIVE INGREDIENTS: SUNFLOWER OIL; YELLOW WAX; TOCOPHEROL

COCOOIL SPF 15

Active ingredients

Octyl methoxycinnamate 7.5%,
Octocrylene 5%, Avobenzone 3%

Purpose

Sunscreen

Uses

• helps prevent sunburn • if used as directed with other sun protection measures (see Directions) decreases the risk of skin cancer and early skin aging caused by the sun.

Warnings

For external use only

Do not use

- on damaged or broken skin

When using this product

- keep out of eyes. Rinse with water to remove

Stop use and ask a doctor

- if rash occurs

Keep out of reach of children

- If this product is swallowed get medical help or contact a Poison Control Centre right away.

Directions

APPLY liberally 15 minutes before sun exposure

- USE a waterresistant sunscreen if sweating or swimming.

Sun Protection Measures. SPENDING time in the sun increases your risk of skin cancer and early skin aging. To decrease risk, regularly use a sunscreen with a broad spectrum SPF of 15 or higher and other sun protection measures including

- LIMIT time in the sun especially between 10 am and 2 pm
- WEAR long sleeved shirts, pants, hats and sunglasses
- REAPPLY at least every 2 hours
- USE a water resistant sunscreen if sweating or swimming
- Children under 6 months ask a doctor.

Other information

• Protect this product from excessive heat and direct sun

Inactive ingredients

HELIANTHUS ANNUUS SEED OIL, Cold pressed Certified Organic COCOS NUCIFERA OIL, BEESWAX, PARFUM, TOCOPHEROL

Questions?

Visit www.cocooil.com.au or call +64 9 361 4191